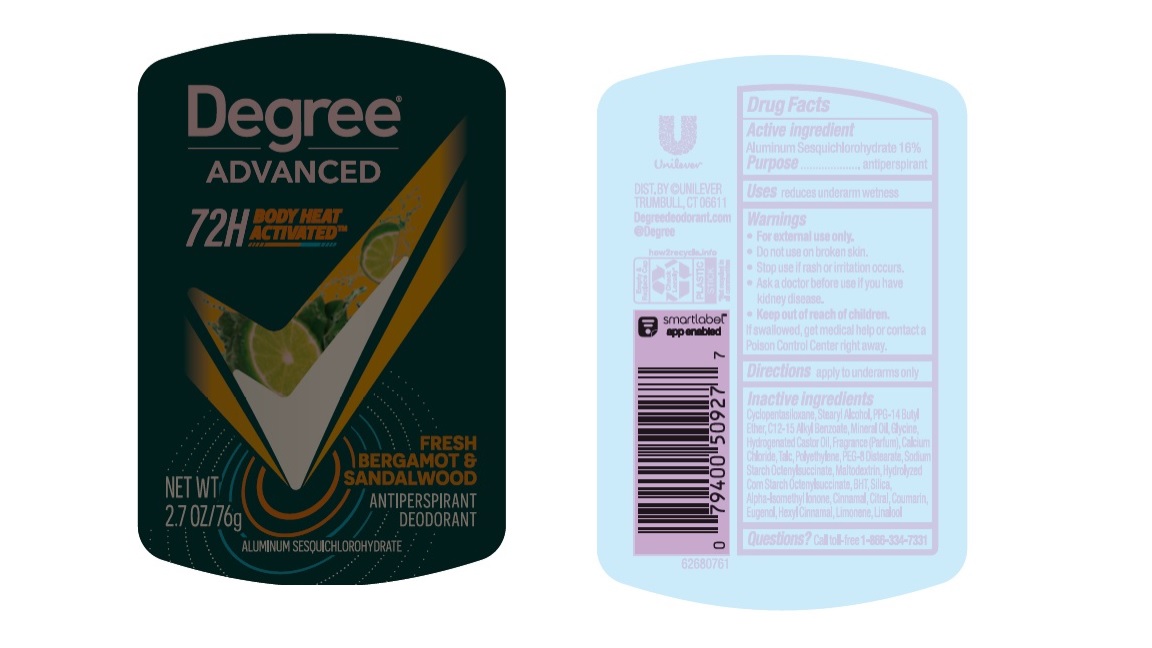 DRUG LABEL: Degree
NDC: 64942-2206 | Form: STICK
Manufacturer: Conopco Inc. d/b/a/ Unilever
Category: otc | Type: HUMAN OTC DRUG LABEL
Date: 20241106

ACTIVE INGREDIENTS: ALUMINUM SESQUICHLOROHYDRATE 16 g/100 g
INACTIVE INGREDIENTS: CINNAMALDEHYDE; CITRAL; MINERAL OIL; HIGH DENSITY POLYETHYLENE; CALCIUM CHLORIDE; GLYCINE; ALKYL (C12-15) BENZOATE; HYDROGENATED CASTOR OIL; CYCLOMETHICONE 5; BUTYLATED HYDROXYTOLUENE; MALTODEXTRIN; PEG-8 DISTEARATE; TALC; SILICON DIOXIDE; PPG-14 BUTYL ETHER; STEARYL ALCOHOL; LIMONENE, (+)-; LINALOOL, (+/-)-; COUMARIN; .ALPHA.-HEXYLCINNAMALDEHYDE; EUGENOL; ISOMETHYL-.ALPHA.-IONONE

Degree Advanced Fresh Bergamot & Sandalwood 72H Antiperspirant Deodorant

Drug Facts

Active ingredient

Aluminum Sesquichlorohydrate (16%)

Purpose

antiperspirant

Uses

reduces underarm wetness

Warnings

• For external use only.
• Do not use on broken skin .
• Ask a doctor before use if you have kidney disease.
• Stop use if rash or irritation occurs.

• Keep out of reach of children.

If swallowed, get medical help or contact a Poison Control Center right away.

Directions

apply to underarms only

Inactive ingredients

Cyclopentasiloxane, Stearyl Alcohol, PPG-14 Butyl Ether, C12-15 Alkyl Benzoate, Mineral Oil, Glycine, Hydrogenated Castor Oil, Fragrance (Parfum), Calcium Chloride, Talc, Polyethylene, PEG-8 Distearate, Sodium Starch Octenylsuccinate, Maltodextrin, Hydrolyzed Corn Starch Octenylsuccinate, BHT, Silica, Alpha-Isomethyl Ionone, Cinnamal, Citral, Coumarin, Eugenol, Hexyl Cinnamal, Limonene. Linalool

Questions?

Call toll-free 1-866-334-7331